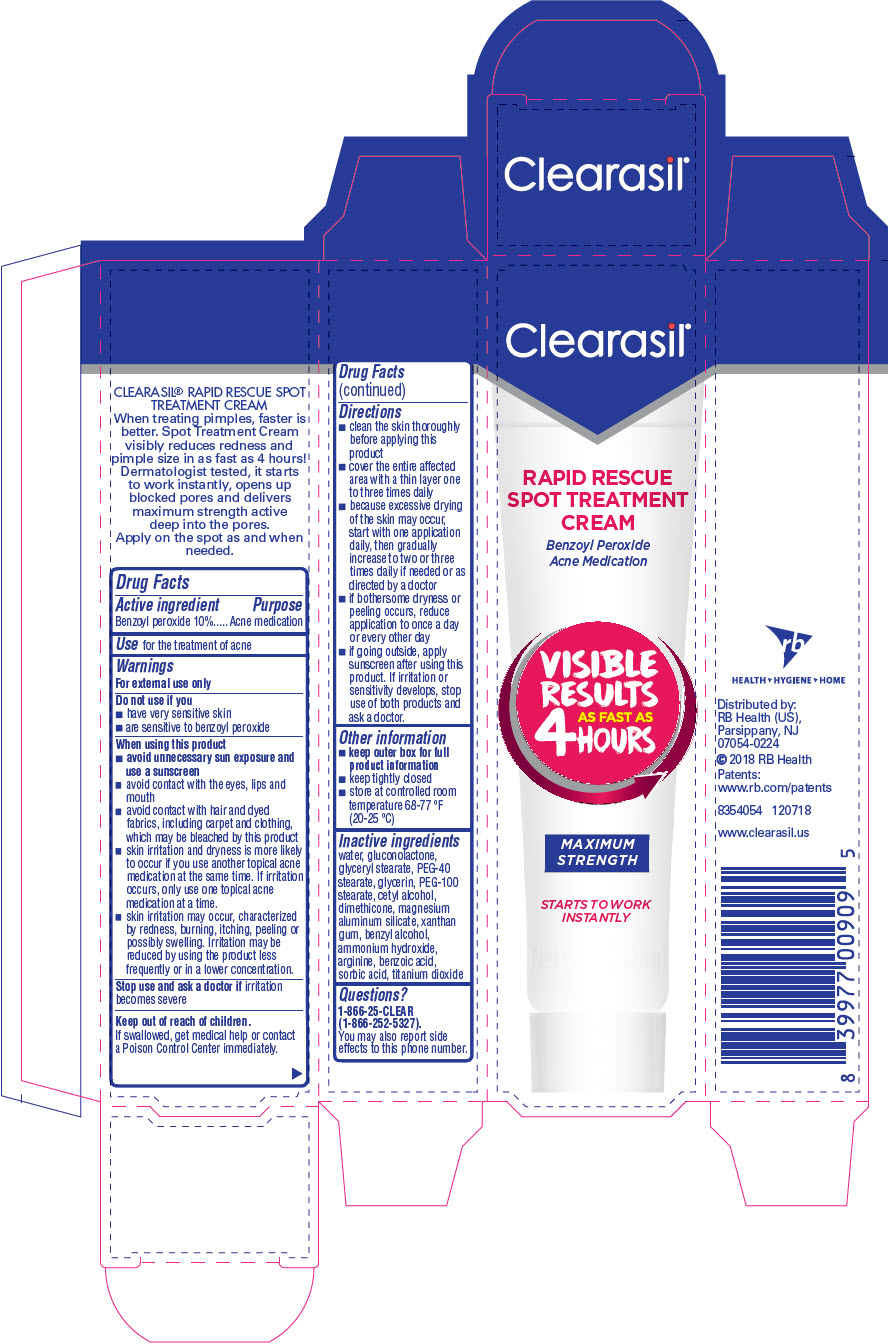 DRUG LABEL: Clearasil Rapid Rescue Spot Treatment
NDC: 63824-433 | Form: CREAM
Manufacturer: RB Health (US) LLC
Category: otc | Type: HUMAN OTC DRUG LABEL
Date: 20241218

ACTIVE INGREDIENTS: BENZOYL PEROXIDE 10 g/100 g
INACTIVE INGREDIENTS: WATER; GLUCONOLACTONE; GLYCERYL MONOSTEARATE; PEG-40 STEARATE; GLYCERIN; PEG-100 STEARATE; CETYL ALCOHOL; DIMETHICONE; MAGNESIUM ALUMINUM SILICATE; XANTHAN GUM; BENZYL ALCOHOL; AMMONIA; ARGININE; BENZOIC ACID; SORBIC ACID; TITANIUM DIOXIDE

Clearasil®Rapid Rescue Spot Treatment Cream

Drug Facts

Active ingredient

Benzoyl peroxide 10%

Purpose

Acne medication

Use

for the treatment of acne

Warnings

For external use only

Do not use if you

- have very sensitive skin
- are sensitive to benzoyl peroxide

When using this product

- avoid unnecessary sun exposure and use a sunscreen
- avoid contact with the eyes, lips and mouth
- avoid contact with hair and dyed fabrics, including carpet and clothing, which may be bleached by this product
- skin irritation and dryness is more likely to occur if you use another topical acne medication at the same time. If irritation occurs, only use one topical acne medication at a time.
- skin irritation may occur, characterized by redness, burning, itching, peeling or possibly swelling. Irritation may be reduced by using the product less frequently or in a lower concentration.

Stop use and ask a doctor ifirritation becomes severe

Keep out of reach of children.If swallowed, get medical help or contact a Poison Control Center immediately.

Directions

- clean the skin thoroughly before applying this product
- cover the entire affected area with a thin layer one to three times daily
- because excessive drying of the skin may occur, start with one application daily, then gradually increase to two or three times daily if needed or as directed by a doctor
- if bothersome dryness or peeling occurs, reduce application to once a day or every other day
- if going outside, apply sunscreen after using this product. If irritation or sensitivity develops, stop use of both products and ask a doctor.

Other information

- keep outer box for full product information
- keep tightly closed
- store at controlled room temperature 68-77 °F (20-25 °C)

Inactive ingredients

Water, Gluconolactone, Glyceryl Stearate, PEG-40 Stearate, Glycerin, PEG-100 Stearate, Cetyl Alcohol, Dimethicone, Magnesium Aluminum Silicate, Xanthan Gum, Benzyl Alcohol, Ammonium Hydroxide, Arginine, Benzoic Acid, Sorbic Acid, Titanium Dioxide

Questions?

1-866-25-CLEAR (1-866-252-5327).

You may also report side effects to this phone number.

Distributed by:
RB Health (US),
Parsippany, NJ
07054-0224

PRINCIPAL DISPLAY PANEL - 28 g Tube Carton

Clearasil®

RAPID RESCUE
SPOT TREATMENT
CREAM

Benzoyl Peroxide
Acne Medication

VISIBLE
RESULTS
AS FAST AS
4 HOURS

MAXIMUM
STRENGTH

STARTS TO WORK
INSTANTLY

Net wt. 1 oz (28 g)